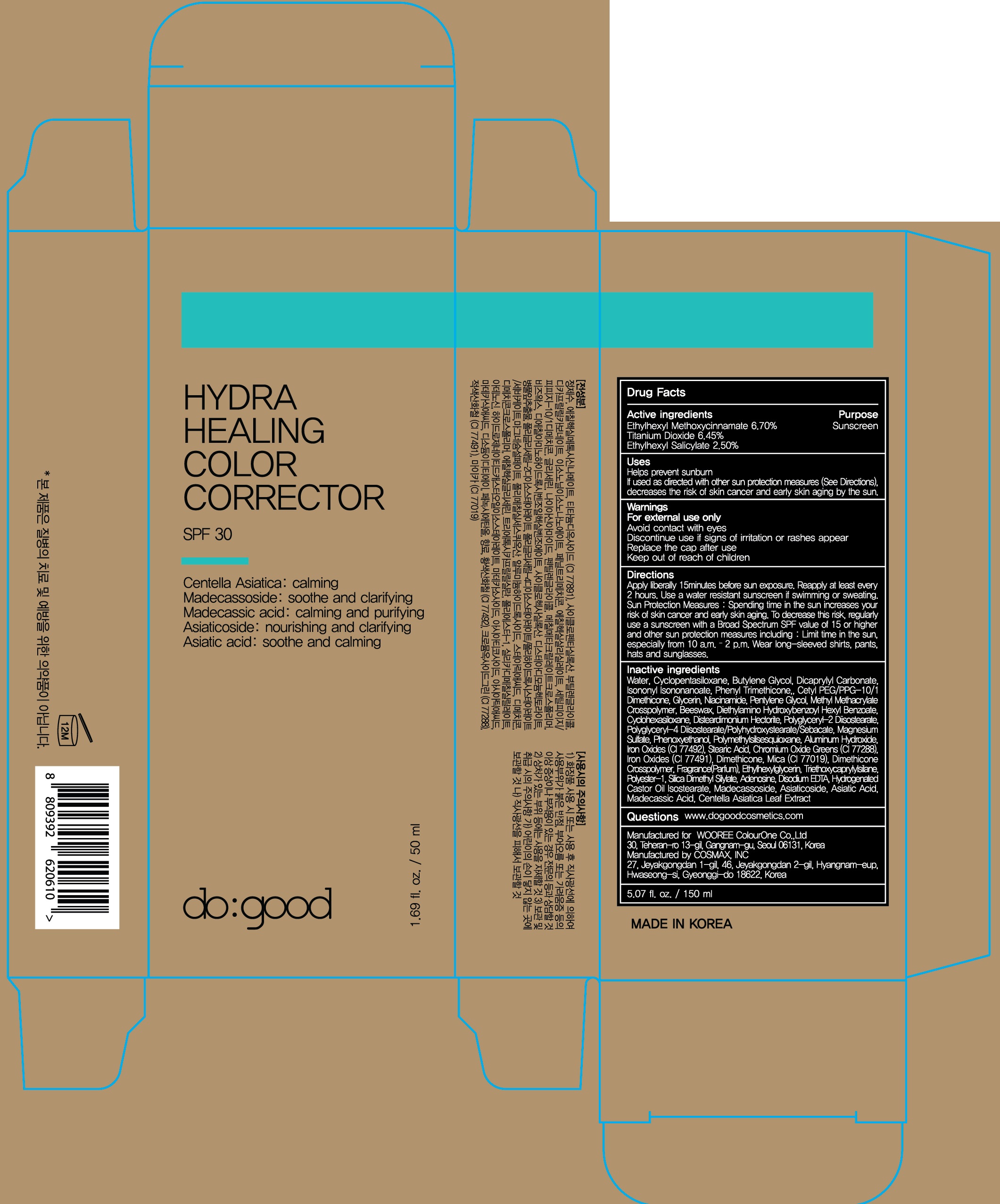 DRUG LABEL: do good Hydra Healing Color Corrector
NDC: 72058-070 | Form: CREAM
Manufacturer: WOOREE Colourone Co.,Ltd
Category: otc | Type: HUMAN OTC DRUG LABEL
Date: 20180226

ACTIVE INGREDIENTS: Octinoxate 3.35 g/50 mL; Titanium Dioxide 3.22 g/50 mL; Octisalate 1.25 g/50 mL
INACTIVE INGREDIENTS: Water; Butylene Glycol

ACTIVE INGREDIENT

Active ingredients: Ethylhexyl Methoxycinnamate 6.70%, Titanium Dioxide 6.45%, Ethylhexyl Salicylate 2.50%

INACTIVE INGREDIENT

Inactive ingredients:

Water, Cyclopentasiloxane, Butylene Glycol, Dicaprylyl Carbonate, Isononyl Isononanoate, Phenyl Trimethicone, Cetyl PEG/PPG-10/1 Dimethicone, Glycerin, Niacinamide, Pentylene Glycol, Methyl Methacrylate Crosspolymer, Beeswax, Cyclohexasiloxane, Disteardimonium Hectorite, Polyglyceryl-2 Diisostearate, Polyglyceryl-4 Diisostearate/Polyhydroxystearate/Sebacate, Magnesium Sulfate, Phenoxyethanol, Polymethylsilsesquioxane, Aluminum Hydroxide, Iron Oxides (CI 77492), Stearic Acid, Chromium Oxide Greens (CI 77288), Iron Oxides (CI 77491), Dimethicone, Mica (CI 77019), Dimethicone Crosspolymer, Fragrance(Parfum), Ethylhexylglycerin, Triethoxycaprylylsilane, Polyester-1, Silica Dimethyl Silylate, Adenosine, Disodium EDTA, Hydrogenated Castor Oil Isostearate, Madecassoside, Asiaticoside, Asiatic Acid, Madecassic Acid, Centella Asiatica Leaf Extract

PURPOSE

Purpose: Sunscreen

WARNINGS

For external use only.

Avoid contact with eyes.

Discontinue use if signs of irritation or rashes appear.

Replace the cap after use.

Keep out of reach of children

DESCRIPTION

Uses:

- Helps prevent sunburn

- If used as directed with other sun protection measures (See Directions), decreases the risk of skin cancer and early skin aging by the sun.

Directions:

Apply liberally 15 minutes before sun exposure

Reapply at least every 2 hours

Use a water resistant sunscreen if swimming or sweating

Sun Protection Measures: Spending time in the sun increases your risk of skin cancer and early skin aging.

To decrease this risk, regularly use a sunscreen with a Broad Spectrum SPF value of 15 or higher and other sun protection measures including: Limit time in the sun, especially from 10 a.m. – 2 p.m.

Wear long-sleeved shirts, pants, hats and sunglasses